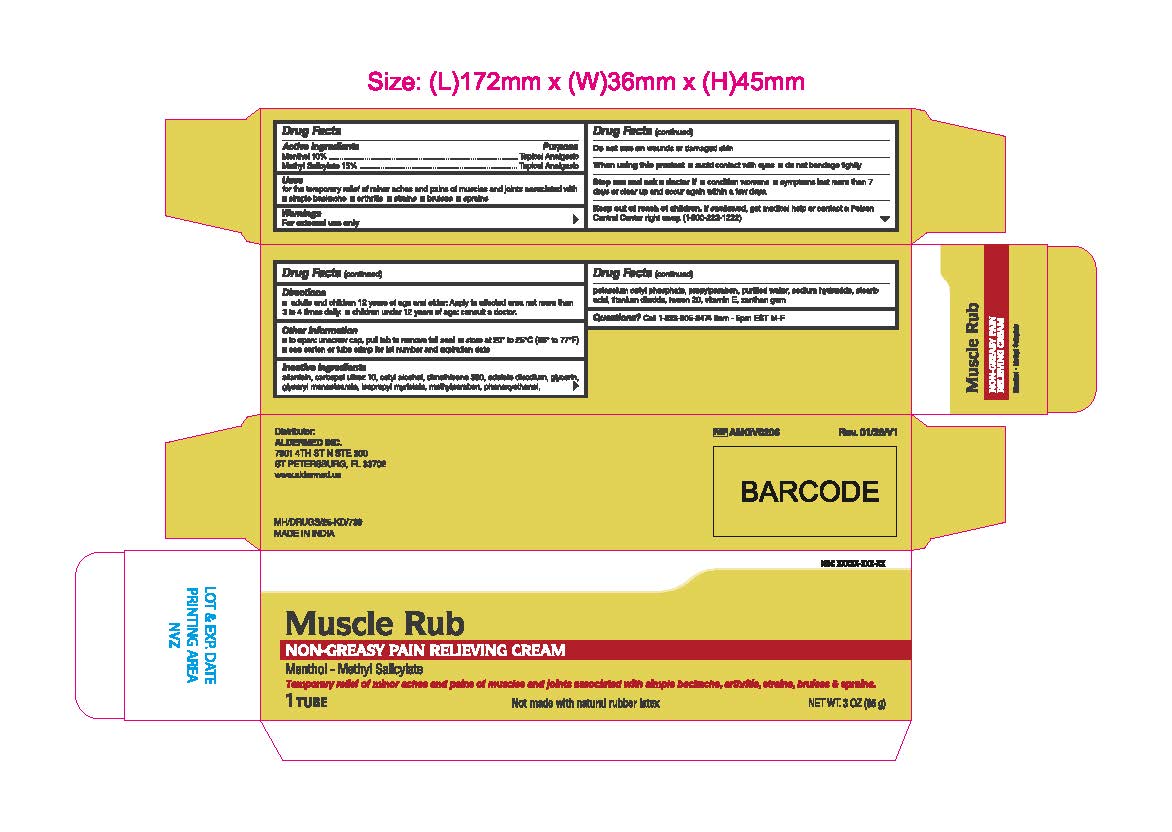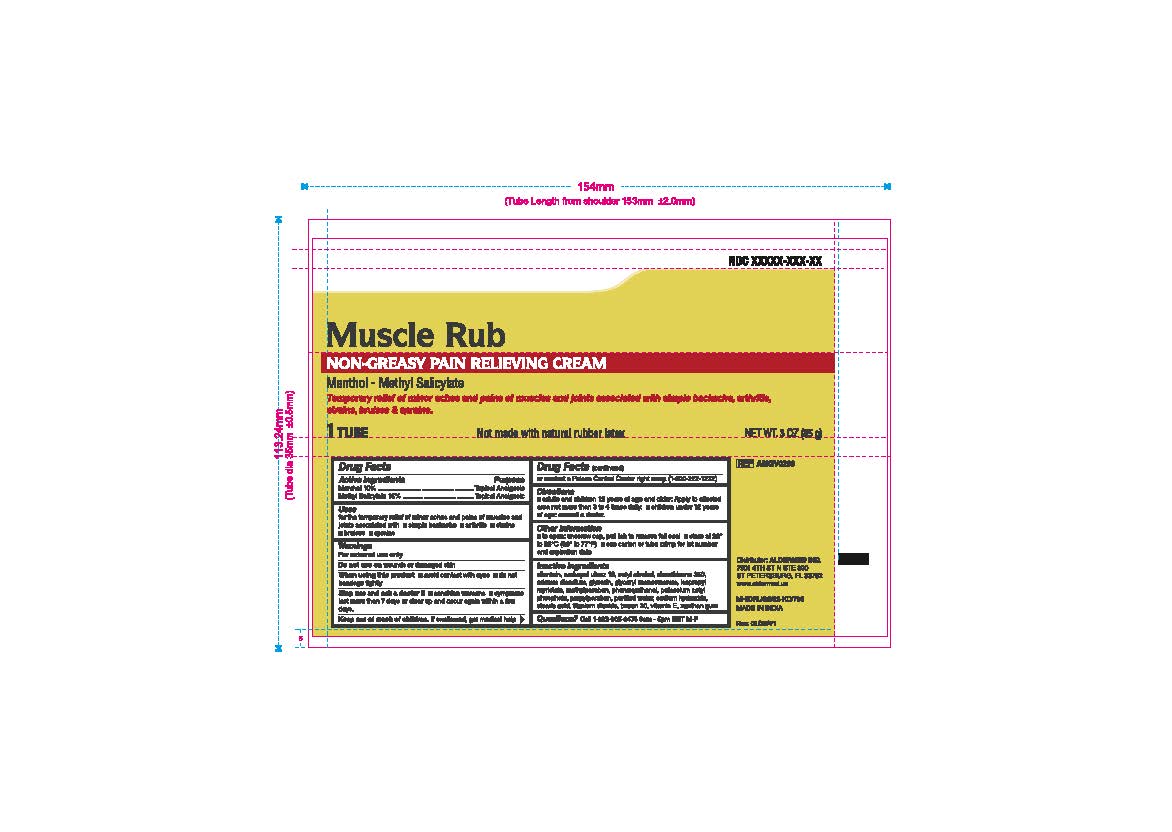 DRUG LABEL: Muscle Rub
NDC: 87236-005 | Form: CREAM
Manufacturer: Aldermed Inc.
Category: otc | Type: HUMAN OTC DRUG LABEL
Date: 20260212

ACTIVE INGREDIENTS: MENTHOL 10 g/100 g; METHYL SALICYLATE 15 g/100 g
INACTIVE INGREDIENTS: ISOPROPYL MYRISTATE; METHYLPARABEN; PHENOXYETHANOL; SODIUM HYDROXIDE; STEARIC ACID; EDETATE DISODIUM ANHYDROUS; WATER; ALLANTOIN; CARBOXYPOLYMETHYLENE; DIMETHICONE; CETYL ALCOHOL; TITANIUM DIOXIDE; ALPHA-TOCOPHEROL ACETATE; XANTHAN GUM; POTASSIUM CETYL PHOSPHATE; PROPYLPARABEN; POLYSORBATE 20; GLYCERIN; GLYCERYL MONOSTEARATE

Muscle Rub

Active Ingredient

Menthol 10%

Methyl Salicylate USP 15%

Purpose

Topical Analgesic

Uses

For the temporary relief of minor aches and pains of muscles and joints associated with simple backache, arthritis, strains, bruises, sprains

Warnings

For external use only

Do not use on

wounds or damaged skin

When using this product

- avoid contact with eyes
- do not bandage tightly

Stop use and ask a doctor if

- condition worsens
- symptoms last more than 7 days or clear up and occur again within a few days

KEEP OUT OF REACH OF CHILDREN

If swallowed, get medical help or contact a Poison Control Center right away. (1-800-222-1222)

Directions

- Adults and children 2 years of age and older: Apply to affected area not more than 3 to 4 times daily
- Children under 2 years of age: Consult a doctor

Other Information

■ Do not use if seal on the tube is damaged or is not visible. To open, unscrew cap, pull tab to remove foil seal ■ Store at room temperature ■ See crimp of tube or carton for Lot Number and Expiry Date

Inactive Ingredients

Allantoin, Carbomer (Ultrez 10), Cetyl Alcohol, Dimethicone, Disodium EDTA, Glycerin, Glyceryl Monostearate, Isopropyl Myristate, Methyl Paraben, Phenoxyethanol, Potassium Cetyl Phosphate, Propyl Paraben, Purified Water, Sodium Hydroxide, Stearic Acid, Titanium Dioxide, Tween 20, Vitamin E, Xanthan Gum

Questions

Call 1-833-605-84-74 9am-5 pm EST M-F